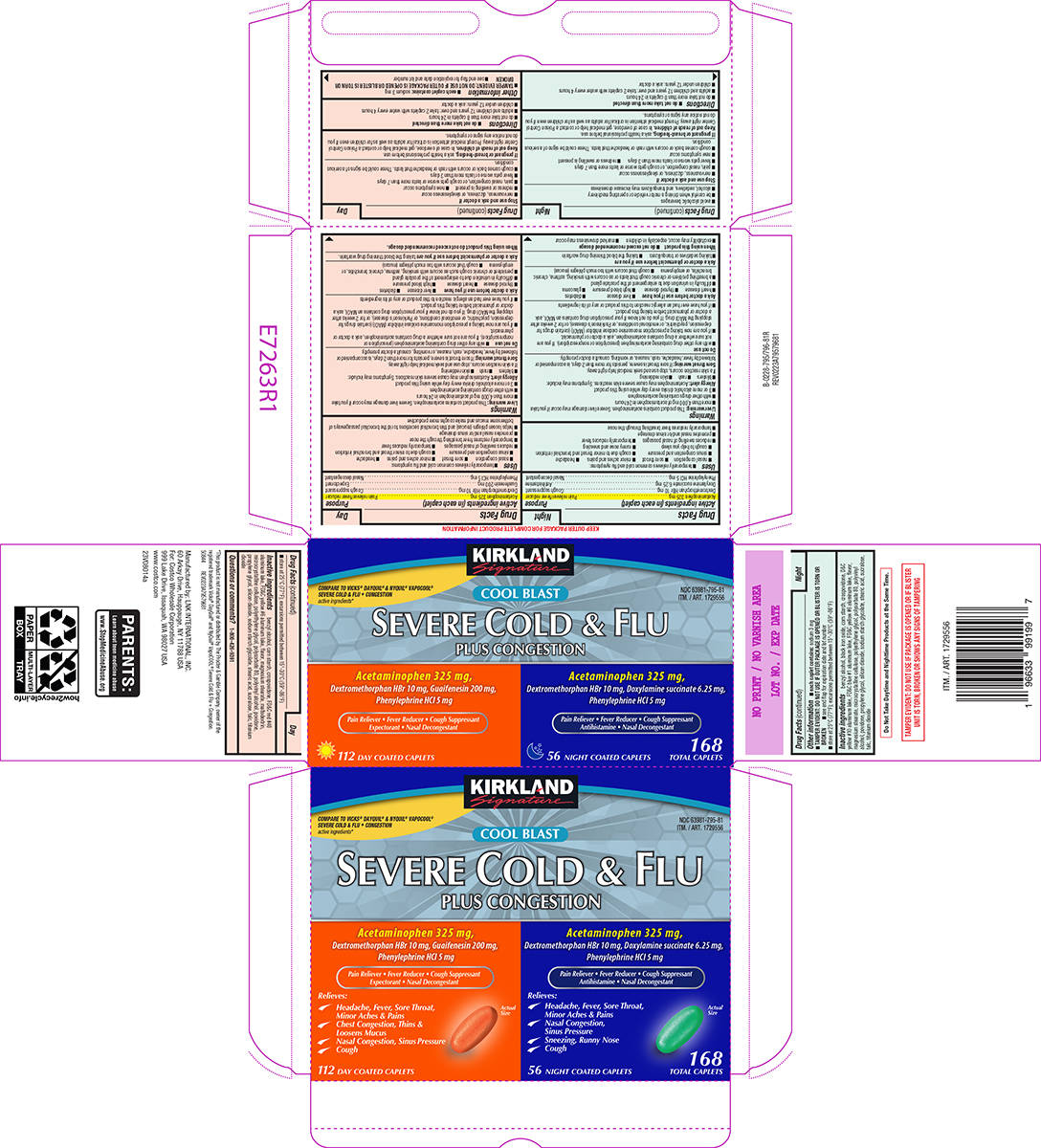 DRUG LABEL: Severe Cold and Flu Plus Congestion
NDC: 63981-795 | Form: KIT | Route: ORAL
Manufacturer: COSTCO WHOLESALE CORPORATION
Category: otc | Type: HUMAN OTC DRUG LABEL
Date: 20250426

ACTIVE INGREDIENTS: ACETAMINOPHEN 325 mg/1 1; DEXTROMETHORPHAN HYDROBROMIDE 10 mg/1 1; GUAIFENESIN 200 mg/1 1; PHENYLEPHRINE HYDROCHLORIDE 5 mg/1 1; ACETAMINOPHEN 325 mg/1 1; DEXTROMETHORPHAN HYDROBROMIDE 10 mg/1 1; DOXYLAMINE SUCCINATE 6.25 mg/1 1; PHENYLEPHRINE HYDROCHLORIDE 5 mg/1 1
INACTIVE INGREDIENTS: BENZYL ALCOHOL; STARCH, CORN; CROSPOVIDONE, UNSPECIFIED; FD&C RED NO. 40 ALUMINUM LAKE; FD&C YELLOW NO. 6 ALUMINUM LAKE; MAGNESIUM STEARATE; MALTODEXTRIN; MICROCRYSTALLINE CELLULOSE; POLYETHYLENE GLYCOL, UNSPECIFIED; POLYSORBATE 80; POLYVINYL ALCOHOL, UNSPECIFIED; POVIDONE, UNSPECIFIED; PROPYLENE GLYCOL; SILICON DIOXIDE; SODIUM STARCH GLYCOLATE TYPE A POTATO; STEARIC ACID; SUCRALOSE; TALC; TITANIUM DIOXIDE; BENZYL ALCOHOL; FERROSOFERRIC OXIDE; STARCH, CORN; CROSPOVIDONE, UNSPECIFIED; D&C YELLOW NO. 10 ALUMINUM LAKE; FD&C BLUE NO. 1 ALUMINUM LAKE; FD&C YELLOW NO. 6 ALUMINUM LAKE; MAGNESIUM STEARATE; MICROCRYSTALLINE CELLULOSE; POLYETHYLENE GLYCOL, UNSPECIFIED; POLYSORBATE 80; POLYVINYL ALCOHOL, UNSPECIFIED; POVIDONE, UNSPECIFIED; PROPYLENE GLYCOL; SILICON DIOXIDE; SODIUM STARCH GLYCOLATE TYPE A POTATO; STEARIC ACID; SUCRALOSE; TALC; TITANIUM DIOXIDE

Kirkland 44-795796-81

Day

Active ingredients (in each caplet)

Acetaminophen 325 mg
Dextromethorphan HBr 10 mg
Guaifenesin 200 mg
Phenylephrine HCl 5 mg

Purpose

Pain reliever/fever reducer
Cough suppressant
Expectorant
Nasal decongestant

Uses

- temporarily relieves common cold and flu symptoms:
  - nasal congestion
  - sore throat
  - minor aches and pains
  - headache
  - sinus congestion and pressure
  - cough due to minor throat and bronchial irritation
  - reduces swelling of nasal passages
- temporarily reduces fever
- temporarily restores freer breathing through the nose
- promotes nasal and/or sinus drainage
- helps loosen phlegm (mucus) and thin bronchial secretions to rid the bronchial passageways of bothersome mucus and make coughs more productive

Warnings

Liver warning: This product contains acetaminophen. Severe liver damage may occur if you take

- more than 4,000 mg of acetaminophen in 24 hours
- with other drugs containing acetaminophen
- 3 or more alcoholic drinks every day while using this product

Allergy alert: Acetaminophen may cause severe skin reactions. Symptoms may include:

- blisters
- rash
- skin reddening

If a skin reaction occurs, stop use and seek medical help right away.

Sore throat warning: If sore throat is severe, persists for more than 2 days, is accompanied or followed by fever, headache, rash, nausea, or vomiting, consult a doctor promptly.

Do not use

- with any other drug containing acetaminophen (prescription or nonprescription). If you are not sure whether a drug contains acetaminophen, ask a doctor or pharmacist.
- if you are now taking a prescription monoamine oxidase inhibitor (MAOI) (certain drugs for depression, psychiatric, or emotional conditions, or Parkinson’s disease), or for 2 weeks after stopping the MAOI drug. If you do not know if your prescription drug contains an MAOI, ask a doctor or pharmacist before taking this product.
- if you have ever had an allergic reaction to this product or any of its ingredients

Ask a doctor before use if you have

- liver disease
- diabetes
- thyroid disease
- heart disease
- high blood pressure
- difficulty in urination due to enlargement of the prostate gland
- persistent or chronic cough such as occurs with smoking, asthma, chronic bronchitis, or emphysema
- cough that occurs with too much phlegm (mucus)

Ask a doctor or pharmacist before use if you are

taking the blood thinning drug warfarin.

When using this product

do not exceed recommended dosage.

Stop use and ask a doctor if

- nervousness, dizziness, or sleeplessness occur
- redness or swelling is present
- new symptoms occur
- pain, nasal congestion, or cough gets worse or lasts more than 7 days
- fever gets worse or lasts more than 3 days
- cough comes back or occurs with rash or headache that lasts. These could be signs of a serious condition.

If pregnant or breast-feeding,

ask a health professional before use.

Keep out of reach of children.

In case of overdose, get medical help or contact a Poison Control Center right away. Prompt medical attention is critical for adults as well as for children even if you do not notice any signs or symptoms.

Directions

- do not take more than directed
- do not take more than 8 caplets in 24 hours
- adults and children 12 years and over: take 2 caplets with water every 4 hours
- children under 12 years: ask a doctor

Other information

- each caplet contains: sodium 3 mg
- TAMPER EVIDENT: DO NOT USE IF OUTER PACKAGE IS OPENED OR BLISTER IS TORN OR BROKEN
- see end flap for expiration date and lot number
- store at 25°C (77°F); excursions permitted between 15°-30°C (59°-86°F)

Inactive ingredients

benzyl alcohol, corn starch, crospovidone, FD&C red #40 aluminum lake, FD&C yellow #6 aluminum lake, flavor, magnesium stearate, maltodextrin, microcrystalline cellulose, polyethylene glycol, polysorbate 80, polyvinyl alcohol, povidone, propylene glycol, silicon dioxide, sodium starch glycolate, stearic acid, sucralose, talc, titanium dioxide

Questions or comments?

1-800-426-9391

Night

Active ingredients (in each caplet)

Acetaminophen 325 mg
Dextromethorphan HBr 10 mg
Doxylamine succinate 6.25 mg
Phenylephrine HCl 5 mg

Purpose

Pain reliever/fever reducer
Cough suppressant
Antihistamine
Nasal decongestant

Uses

- temporarily relieves common cold and flu symptoms:
  - nasal congestion
  - sore throat
  - minor aches and pains
  - headache
  - sinus congestion and pressure
  - cough due to minor throat and bronchial irritation
  - cough to help you sleep
  - runny nose and sneezing
- reduces swelling of nasal passages
- temporarily reduces fever
- promotes nasal and/or sinus drainage
- temporarily restores freer breathing through the nose

Warnings

Liver warning: This product contains acetaminophen. Severe liver damage may occur if you take

- more than 4,000 mg of acetaminophen in 24 hours
- with other drugs containing acetaminophen
- 3 or more alcoholic drinks every day while using this product

Allergy alert: Acetaminophen may cause severe skin reactions. Symptoms may include:

- blisters
- rash
- skin reddening

If a skin reaction occurs, stop use and seek medical help right away.

Sore throat warning: If sore throat is severe, persists for more than 2 days, is accompanied or followed by fever, headache, rash, nausea, or vomiting, consult a doctor promptly.

Do not use

- with any other drug containing acetaminophen (prescription or nonprescription). If you are not sure whether a drug contains acetaminophen, ask a doctor or pharmacist.
- if you are now taking a prescription monoamine oxidase inhibitor (MAOI) (certain drugs for depression, psychiatric, or emotional conditions, or Parkinson’s disease), or for 2 weeks after stopping the MAOI drug. If you do not know if your prescription drug contains an MAOI, ask a doctor or pharmacist before taking this product.
- if you have ever had an allergic reaction to this product or any of its ingredients

Ask a doctor before use if you have

- liver disease
- diabetes
- heart disease
- thyroid disease
- high blood pressure
- glaucoma
- difficulty in urination due to enlargement of the prostate gland
- a breathing problem or chronic cough that lasts or as occurs with smoking, asthma, chronic bronchitis, or emphysema
- cough that occurs with too much phlegm (mucus)

Ask a doctor or pharmacist before use if you are

- taking sedatives or tranquilizers
- taking the blood thinning drug warfarin

When using this product

- do not exceed recommended dosage
- excitability may occur, especially in children
- marked drowsiness may occur
- avoid alcoholic beverages
- be careful when driving a motor vehicle or operating machinery
- alcohol, sedatives, and tranquilizers may increase drowsiness

Stop use and ask a doctor if

- nervousness, dizziness, or sleeplessness occur
- pain, nasal congestion, or cough gets worse or lasts more than 7 days
- fever gets worse or lasts more than 3 days
- redness or swelling is present
- new symptoms occur
- cough comes back or occurs with rash or headache that lasts. These could be signs of a serious condition.

If pregnant or breast-feeding,

ask a health professional before use.

Keep out of reach of children.

In case of overdose, get medical help or contact a Poison Control Center right away. Prompt medical attention is critical for adults as well as for children even if you do not notice any signs or symptoms.

Directions

- do not take more than directed
- do not take more than 8 caplets in 24 hours
- adults and children 12 years and over: take 2 caplets with water every 4 hours
- children under 12 years: ask a doctor

Other information

- each caplet contains: sodium 3 mg
- TAMPER EVIDENT: DO NOT USE IF OUTER PACKAGE IS OPENED OR BLISTER IS TORN OR BROKEN
- see end flap for expiration date and lot number
- store at 25°C (77°F); excursions permitted between 15°-30°C (59°-86°F)

Inactive ingredients

benzyl alcohol, black iron oxide, corn starch, crospovidone, D&C yellow #10 aluminum lake, FD&C blue #1 aluminum lake, FD&C yellow #6 aluminum lake, flavor, magnesium stearate, microcrystalline cellulose, polyethylene glycol, polysorbate 80, polyvinyl alcohol, povidone, propylene glycol, silicon dioxide, sodium starch glycolate, stearic acid, sucralose, talc, titanium dioxide

Principal display panel

KIRKLAND
Signature

COMPARE TO VICKS® DAYQUIL® & NYQUIL® VAPOCOOL®
SEVERE COLD & FLU + CONGESTION
active ingredients*

NDC 63981-795-81
ITM. / ART. 1729556

COOL BLAST
SEVERE COLD & FLU
PLUS CONGESTION

Acetaminophen 325 mg,
Dextromethorphan HBr 10 mg, Guaifenesin 200 mg,
Phenylephrine HCl 5 mg

Pain Reliever • Fever Reducer • Cough Suppressant
Expectorant • Nasal Decongestant

Relieves:
Headache, Fever, Sore Throat,
Minor Aches & Pains
Chest Congestion, Thins &
Loosens Mucus
Nasal Congestion, Sinus Pressure
Cough

Actual
Size

112 DAY COATED CAPLETS

Acetaminophen 325 mg,
Dextromethorphan HBr 10 mg, Doxylamine succinate 6.25 mg,
Phenylephrine HCl 5 mg

Pain Reliever • Fever Reducer • Cough Suppressant
Antihistamine • Nasal Decongestant

Relieves:
Headache, Fever, Sore Throat,
Minor Aches & Pains
Nasal Congestion,
Sinus Pressure
Sneezing, Runny Nose
Cough

Actual
Size

56 NIGHT COATED CAPLETS

168
TOTAL CAPLETS

TAMPER EVIDENT: DO NOT USE IF PACKAGE IS OPENED OR IF BLISTER
UNIT IS TORN, BROKEN OR SHOWS ANY SIGNS OF TAMPERING

Do Not Take Daytime and Nighttime Products at the Same Time.

*This product is not manufactured or distributed by The Procter & Gamble Company, owner of the
registered trademark Vicks® DayQuil® and NyQuil® VapoCOOL® Severe Cold & Flu + Congestion.
50844 REV0223A79579681

Manufactured by: LNK INTERNATIONAL, INC.
60 Arkay Drive, Hauppauge, NY 11788 USA
For: Costco Wholesale Corporation
999 Lake Drive, Issaquah, WA 98027 USA
www.costco.com

23V08014a

Kirkland 44-795796